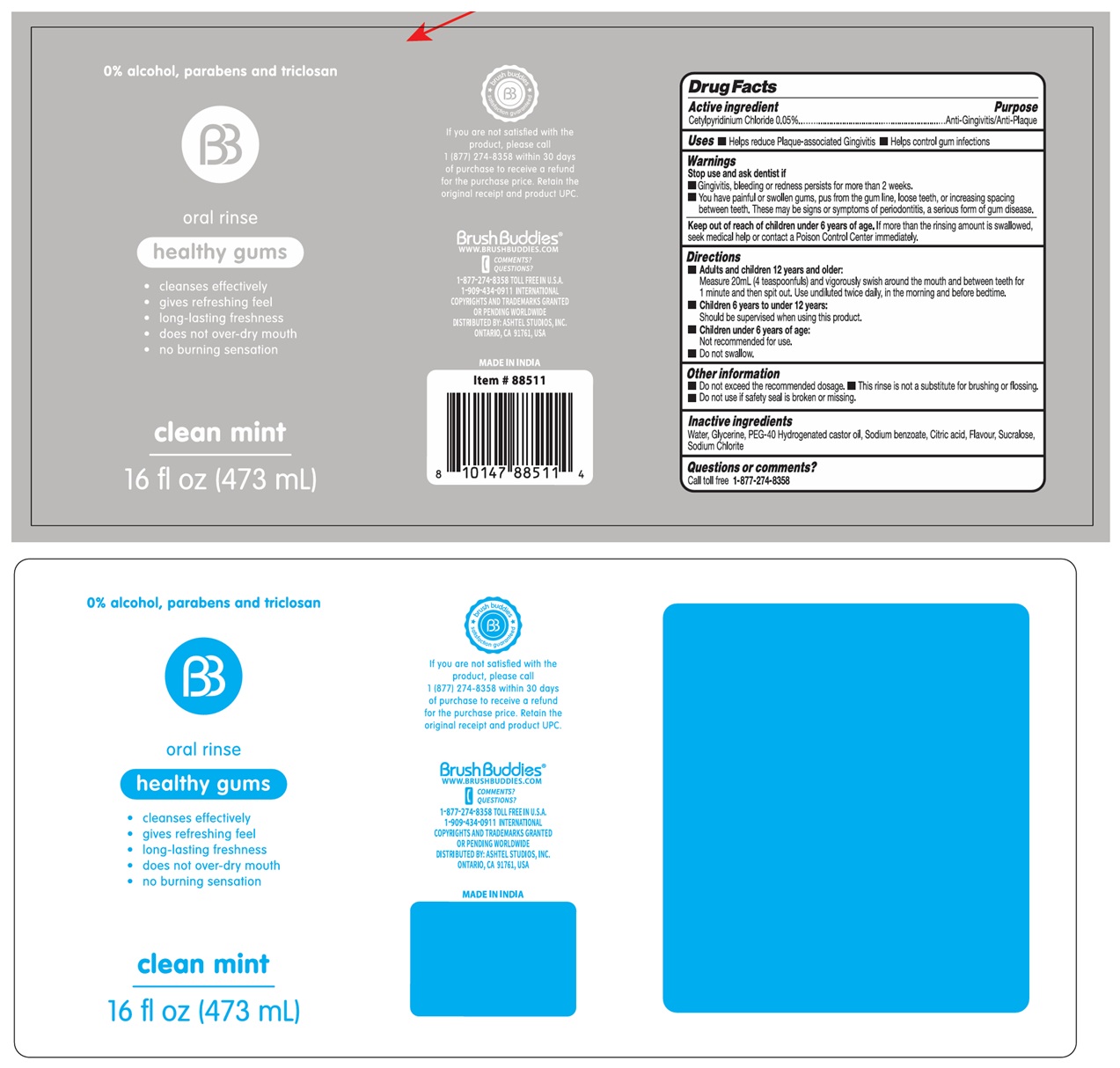 DRUG LABEL: Brush Buddies oral rinse - healthy gums
NDC: 70108-278 | Form: MOUTHWASH
Manufacturer: Ashtel Studios, Inc.
Category: otc | Type: HUMAN OTC DRUG LABEL
Date: 20260103

ACTIVE INGREDIENTS: CETYLPYRIDINIUM CHLORIDE 0.05 g/100 mL
INACTIVE INGREDIENTS: WATER; GLYCERIN; POLYOXYL 40 HYDROGENATED CASTOR OIL; SODIUM BENZOATE; CITRIC ACID MONOHYDRATE; SUCRALOSE; SODIUM CHLORITE

Brush Buddies® oral rinse healthy gums

Active ingredient

Cetylpyridinium Chloride 0.05%

Purpose

Anti-Gingivitis/Anti-Plaque

Uses

• Helps reduce Plaque-associated Gingivitis • Helps control gum infections

Warnings

Stop use and ask dentist if
• Gingivitis, bleeding or redness persists for more than 2 weeks.
• You have painful or swollen gums, pus from the gum line, loose teeth, or increasing spacing between teeth. These may be signs or symptoms of periodontitis, a serious form of gum disease.

Keep out of reach of children under 6 years of age. If more than the rinsing amount is swallowed, seek medical help or contact a Poison Control Center immediately.

Directions

• Adults and children 12 years and older:
Measure 20mL (4 teaspoonfuls) and vigorously swish around the mouth and between teeth for 1 minute and then spit out. Use undiluted twice daily, in the morning and before bedtime.

• Children 6 years to under 12 years:
Should be supervised when using this product.

• Children under 6 years of age:
Not recommended for use.

• Do not swallow.

Other information

• Do not exceed the recommended dosage. • This rinse is not a substitute for brushing or flossing.
• Do not use if safety seal is broken or missing.

Inactive ingredients

Water, Glycerine, PEG-40 Hydrogenated castor oil, Sodium benzoate, Citric acid, Flavour, Sucralose, Sodium Chlorite

Questions or comments?

Call toll free 1-877-274-8358

0% alcohol, parabens and triclosan

• cleanses effectively
• gives refreshing feel
• long-lasting freshness
• does not over-dry mouth
• no burning sensation

clean mint

brush buddies satisfaction guaranteed

If you are not satisfied with the product, please call 1 (877) 274-8358 within 30 days of purchase to receive a refund for the purchase price. Retain the original receipt and product UPC

WWW.BRUSHBUDDIES.COM

1-909-434-0911 INTERNATIONAL

COPYRIGHTS AND TRADEMARKS GRANTED OR PENDING WORLDWIDE
DISTRIBUTED BY: ASHTEL STUDIOS, INC.
ONTARIO, CA 91761, USA

MADE IN INDIA